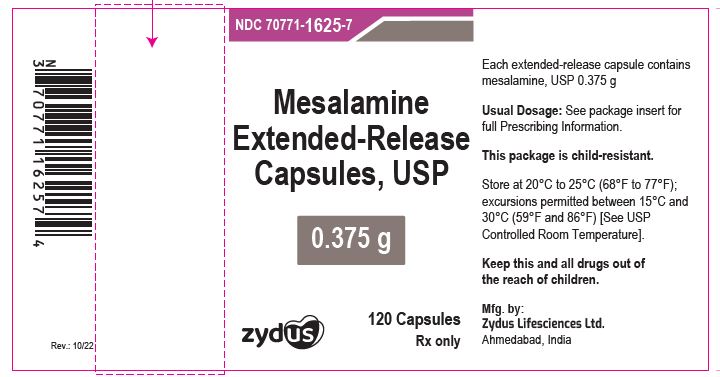 DRUG LABEL: Mesalamine
NDC: 70771-1625 | Form: CAPSULE, EXTENDED RELEASE
Manufacturer: Zydus Lifesciences Limited
Category: prescription | Type: HUMAN PRESCRIPTION DRUG LABEL
Date: 20241130

ACTIVE INGREDIENTS: MESALAMINE 0.375 g/1 1
INACTIVE INGREDIENTS: ETHYLCELLULOSE (10 MPA.S); HYPROMELLOSE 2910 (5 MPA.S); METHACRYLIC ACID - METHYL METHACRYLATE COPOLYMER (1:1); TALC; TRIETHYL CITRATE; FD&C BLUE NO. 1; GELATIN; WATER; SODIUM LAURYL SULFATE; TITANIUM DIOXIDE; FERROSOFERRIC OXIDE; POTASSIUM HYDROXIDE; PROPYLENE GLYCOL; SHELLAC; SUCROSE; STARCH, CORN

MESALAMINE Extended-Release Capsules

PACKAGE LABEL.PRINCIPAL DISPLAY PANEL

Mesalamine Extended-Release Capsules, 0.375 g

120 capsules

NDC 70771-1625-7

Rx only